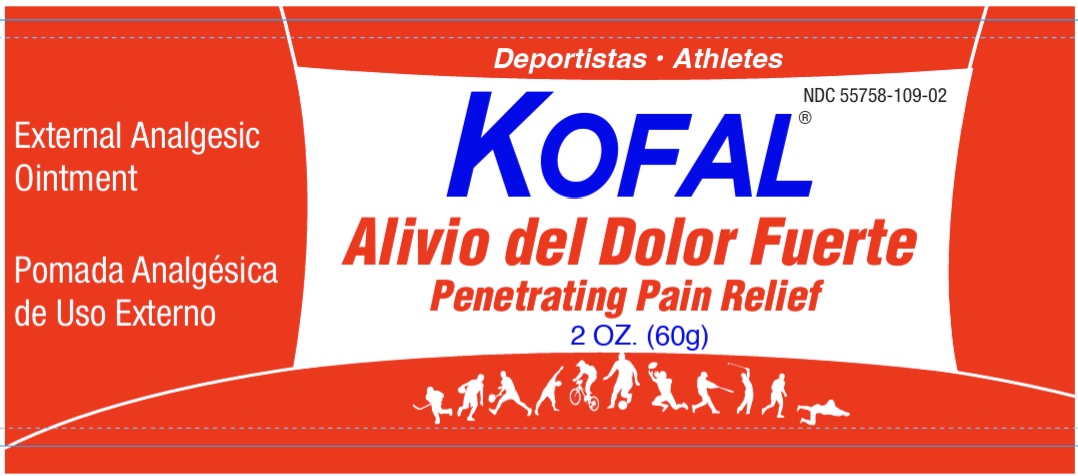 DRUG LABEL: Kofal
NDC: 55758-109 | Form: OINTMENT
Manufacturer: Pharmadel LLC
Category: otc | Type: HUMAN OTC DRUG LABEL
Date: 20251204

ACTIVE INGREDIENTS: METHYL SALICYLATE 10.5 g/100 g
INACTIVE INGREDIENTS: CAMPHOR, (-)-; MENTHOL, UNSPECIFIED FORM; D&C YELLOW NO. 11; PARAFFIN; PROPYLPARABEN; PETROLATUM; LANOLIN

Kofal Fuerte Ointment 2 oz (WP)(DA)

Active Ingredient and Purpose

Active ingredient Purpose

Methyl salicylate 10.5%....................External analgesic

Uses

For the temporary relief of minor aches and pains of muscles and joints associated with

- simple backache
- arthritis
- strains
- sprains

Warnings

For external use only. Avoid contact with the eyes.

Do not use

- on wounds or damaged skin

When using this product

- do not bandage tightly

Stop use and ask a doctor if

- condition worsens
- symptoms persist for more than 7 days or clear up and occurs again within a few days

If pregnant or breast feeding,

ask a health professional before use.

Keep out of reach of children.

If swallowed, get medical help, or contact a Poison Control Center immediately.

Directions

- adults and children 12 years of age and older: apply to affected area not more than 3 to 4 times daily
- children under 12 years of age: do not use, consult a doctor

Other information

- store between 59-86°F (15-30°C)
- do not use if seal over cap is broken, torn, or missing

Inactive ingredients

- camphor, D&C yellow #11, lanolin, menthol, paraffin, petrolatum, propylparaben

Questions or comments?

+1-866-359-3478 M-F 9 AM - 5 PM EST or www.pharmadel.com